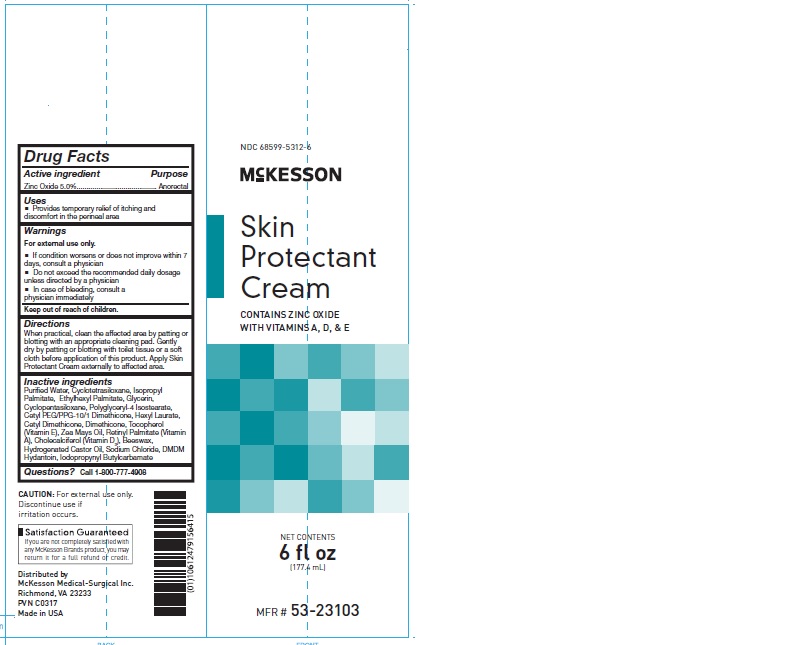 DRUG LABEL: McKesson Skin Protectant
NDC: 68599-5312 | Form: CREAM
Manufacturer: McKesson Medical-Surgical Inc.
Category: otc | Type: HUMAN OTC DRUG LABEL
Date: 20241011

ACTIVE INGREDIENTS: ZINC OXIDE 50 mg/1 mL
INACTIVE INGREDIENTS: CETYL DIMETHICONE 25; DIMETHICONE; TOCOPHEROL; CORN OIL; VITAMIN A PALMITATE; CHOLECALCIFEROL; YELLOW WAX; HYDROGENATED CASTOR OIL; SODIUM CHLORIDE; DIAZOLIDINYL UREA; METHYLPARABEN; WATER; CYCLOMETHICONE 4; CYCLOMETHICONE 5; MINERAL OIL; ISOPROPYL PALMITATE; POLYGLYCERYL-4 ISOSTEARATE; CETYL PEG/PPG-10/1 DIMETHICONE (HLB 2); HEXYL LAURATE; ETHYLHEXYL PALMITATE; GLYCERIN

Skin Protectant Cream

Active ingredient

Zinc Oxide 5.0%

Purpose

Anorectal

Uses

Provides temporary relief of itching and discomfort in the perineal area

Warnings

For external use only.

If condition worsens or does not improve within 7 days, consult a physician

Do not exceed the recommended daily dosage unless directed by a physician

In case of bleeding, consult a physician immediately

Keep out of reach of children.

Directions

When practical, clean the affected area by patting or blotting with an appropriate cleaning pad.

Gently dry by patting or blotting with toilet tissue or a soft cloth before application of this product.

Apply Skin Protectant Cream externally to affected area.

Inactive ingredients

Purified Water, Cyclotetrasiloxane, Isopropyl Palmitate, Ethylhexyl Palmitate, Glycerin, Cyclopentasiloxane, Polyglyceryl-4 Isostearate,
Cetyl PEG/PPG-10/1 Dimethicone, Hexyl Laurate, Cetyl Dimethicone, Dimethicone, Tocopherol (Vitamin E), Zea Mays Oil, Retinyl Palmitate (Vitamin A), Cholecalciferol (Vitamin D3), Beeswax, Hydrogenated Castor Oil, Sodium Chloride, DMDM Hydantoin, Iodopropynyl Butylcarbamate

Questions? Call 1-800-777-4908

PACKAGE LABEL

NDC 68599-5312-6

McKesson

Skin

Protectant

Cream

Contains Zinc Oxide

with Vitamins A, D, and E

NET CONTENTS

6 oz

(177 ml)

MFR # 53-23103